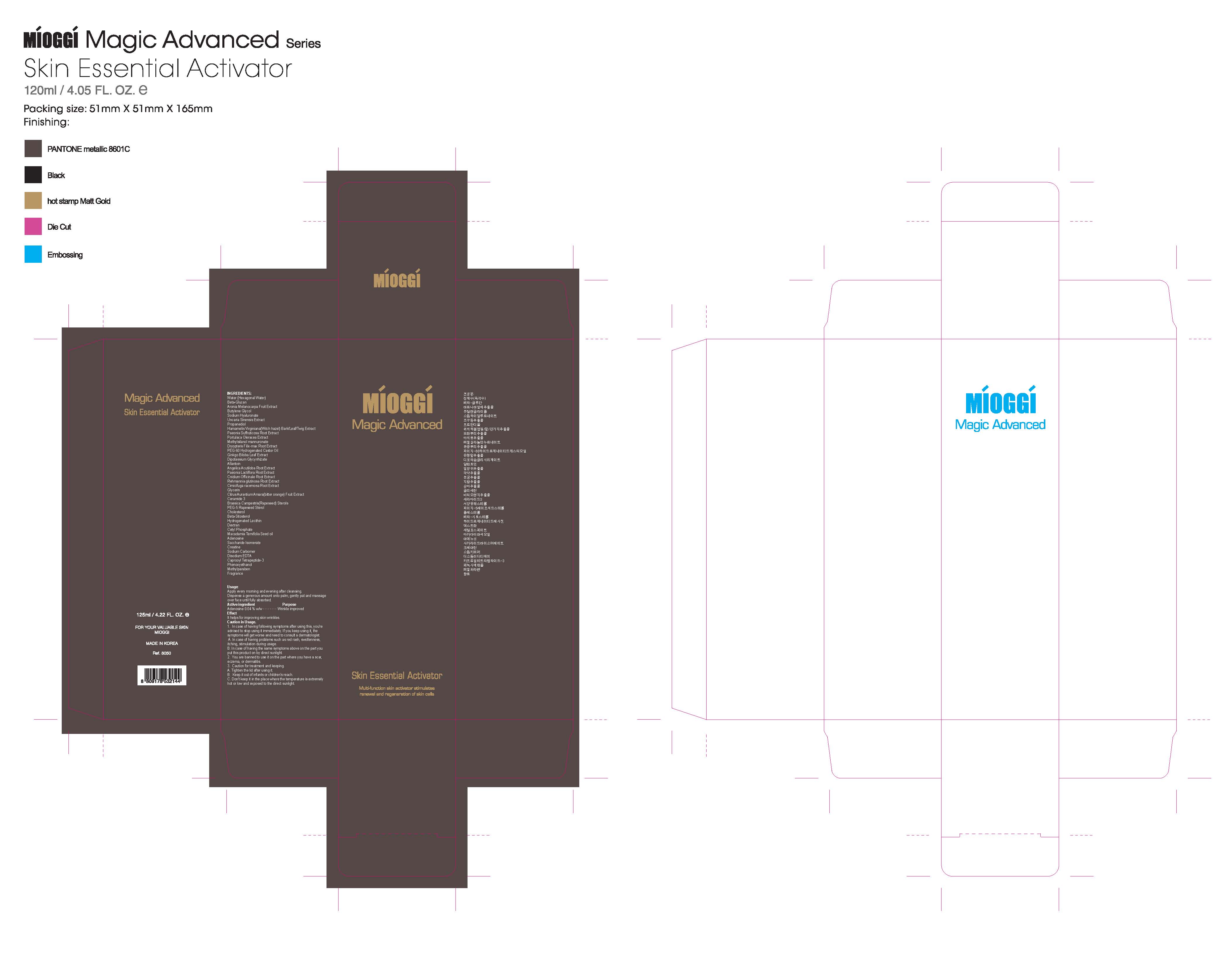 DRUG LABEL: MIOGGI Magic Advanced Skin Essential Activator
                
NDC: 53009-2001 | Form: LIQUID
Manufacturer: Colorpink R&D Inc.
Category: otc | Type: HUMAN OTC DRUG LABEL
Date: 20120820

ACTIVE INGREDIENTS: ADENOSINE 0.05 mg/125 mL
INACTIVE INGREDIENTS: BUTYLENE GLYCOL; PROPANEDIOL; POLYOXYL 60 CASTOR OIL; MORUS ALBA ROOT; DIOSPYROS KAKI LEAF; GREEN TEA LEAF; ALOE VERA LEAF; GLYCYRRHIZINATE DIPOTASSIUM; ALLANTOIN; HYALURONATE SODIUM; UNCARIA SINENSIS WHOLE; PORTULACA OLERACEA WHOLE; PAEONIA LACTIFLORA ROOT; WITCH HAZEL; GINKGO; BITTER ORANGE OIL; REHMANNIA GLUTINOSA ROOT; PAEONIA SUFFRUTICOSA ROOT BARK; DRYOPTERIS CRASSIRHIZOMA WHOLE; DRYOPTERIS FILIX-MAS ROOT; CNIDIUM OFFICINALE ROOT; BLACK COHOSH; ANGELICA ACUTILOBA ROOT; MACADAMIA NUT; MEDIUM-CHAIN TRIGLYCERIDES; GLYCERIN; CHOLESTEROL; RAPESEED STEROL; .BETA.-SITOSTEROL; SACCHARIDE ISOMERATE; HYDROGENATED SOYBEAN LECITHIN; CERAMIDE 3; CHOLETH-24; CETETH-24; ARONIA MELANOCARPA FRUIT; DEXTRAN 40; CREATINE; CETYL PHOSPHATE; CAPROOYL TETRAPEPTIDE-3; CARTHAMUS TINCTORIUS SEEDCAKE; PHENOXYETHANOL; METHYLPARABEN; PROPYLPARABEN; BUTYLATED HYDROXYTOLUENE

Drug Facts

ACTIVE INGREDIENT

ADENOSINE

INACTIVE INGREDIENT

Water, Methylsilanol mannuronate, Beta-glucan, Butylene glycol, Propanediol, PEG-60 hydrogenated castor oil, Morus alba root extract, Diospyros kaki leaf extract, Camellia sinensis leaf extract, Aloe barbadensis leaf extract, Dipotassium glycyrrhizate, Allantoin, Sodium hyaluronate, Adenosine, Sodium carbomer, Uncaria sinensis extract, Portulaca oleracea extract, Paeonia lactiflora root extract, Hamamelis virginiana(Witch hazel) bark/leaf/twig extract, Ginkgo biloba leaf extract, Citrus aurantium amara (Bitter orange) fruit extract, Rehmannia glutinosa root extract, Paeonia suffruticosa bark extract, Dryopteris crassirhizoma extract, Dryopteris filix-mas root extract, Cnidium officinale root extract, Cimicifuga racemosa root extract, Angelica acutiloba root extract, Macadamia ternifolia seed oil, Caprylic/capric triglyceride, Glycerin, PEG-5 rapeseed sterol, Cholesterol, Brassica campestris (Rapeseed) sterols, Beta-sitosterol, Saccharide isomerate, Hydrogenated lecithin, Ceramide 3, Choleth-24, Ceteth-24, Aronia melanocarpa fruit extract, Dextran, Polyglutamic acid, Creatine, Cetyl phosphate, Caprooyl tetrapeptide-3, Carthamus tinctorius (Safflower) seed extract, Disodium EDTA, Phenoxyethanol, Methylparaben, Proplyparaben, BHT, Fragrance

PURPOSE

for improving skin wrinkles

keep out of reach of the children

INDICATIONS AND USAGE

Apply every morning and evening after cleansing.
Dispense a generous amount onto palm, gently pat and massage over face until fully absorbed

WARNINGS

1. In case of having following symptoms after using this, you're advised to stop using it immediately. If you keep using it, the symptoms will get worse and need to consult a dermatologist.
A. In case of having problems such as red rash, swollenness, itching, stimulation during usage.
B. In case of having the same symptoms above on the part you put this product on by direct sunlight.
2. You are banned to use it on the part where you have a scar, eczema, or dermatitis.
3. Caution for treatment and keeping.
A. Tighten the lid after using it.
B. Keep it out of infants or children's reach.
C. Don't keep it in the place where the temperature is extremely hot or low and exposed to the direct sunlight.

DOSAGE AND ADMINISTRATION

- for external use only